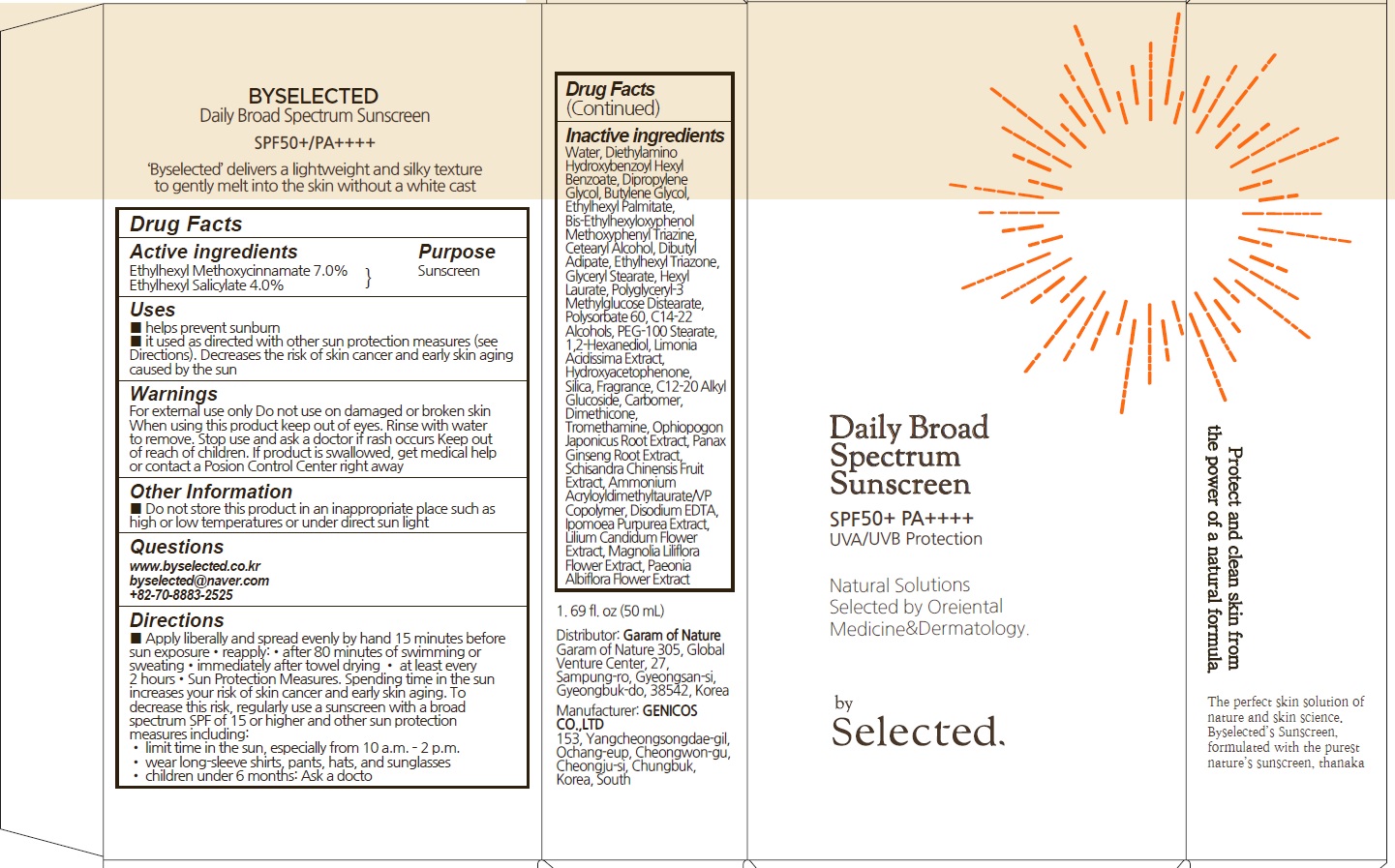 DRUG LABEL: by Selected Daily Broad Spectrum Sunscreen
NDC: 73509-050 | Form: CREAM
Manufacturer: Garam Of Nature
Category: otc | Type: HUMAN OTC DRUG LABEL
Date: 20210803

ACTIVE INGREDIENTS: OCTINOXATE 3.5 g/50 mL; OCTISALATE 2.0 g/50 mL
INACTIVE INGREDIENTS: Water; Dipropylene Glycol

ACTIVE INGREDIENTS

Ethylhexyl Methoxycinnamate 7.0%
Ethylhexyl Salicylate 4.0%

INACTIVE INGREDIENTS

Water, Diethylamino Hydroxybenzoyl Hexyl Benzoate, Dipropylene Glycol, Butylene Glycol, Ethylhexyl Palmitate, Bis-Ethylhexyloxyphenol Methoxyphenyl Triazine, Cetearyl Alcohol, Dibutyl Adipate, Ethylhexyl Triazone, Glyceryl Stearate, Hexyl Laurate, olyglyceryl-3 Methylglucose Distearate, Polysorbate 60, C14-22 Alcohols, PEG-100 Stearate, 1,2-Hexanediol, Limonia Acidissima Extract, Hydroxyacetophenone, Silica, Fragrance, C12-20 Alkyl Glucoside, Carbomer, Dimethicone, Tromethamine, Ophiopogon Japonicus Root Extract, Panax Ginseng Root Extract, Schisandra Chinensis Fruit Extract, Ammonium Acryloyldimethyltaurate/VP Copolymer, Disodium EDTA,
Ipomoea Purpurea Extract, Lilium Candidum Flower Extract, Magnolia Liliflora Flower Extract, Paeonia Albiflora Flower Extract

PURPOSE

Sunscreen

WARNINGS

For external use only

Do not use on damaged or broken skin
When using this product keep out of eyes. Rinse with water to remove.

Stop use and ask a doctor if rash occurs

Keep out of reach of children. If product is swallowed, get medical help or contact a Posion Control Center right away

KEEP OUT OF REACH OF CHILDREN

If product is swallowed, get medical help or contact a Posion Control Center right away

Uses

■ helps prevent sunburn
■ it used as directed with other sun protection measures (see Directions). Decreases the risk of skin cancer and early skin aging caused by the sun

Directions

■ Apply liberally and spread evenly by hand 15 minutes before sun exposure•reapply:•after 80 minutes of swimming or sweating•immediately after towel drying • at least every 2 hours•Sun Protection Measures. Spending time in the sun increases your risk of skin cancer and early skin aging. To decrease this risk, regularly use a sunscreen with a broad spectrum SPF of 15 or higher and other sun protection measures including:
• limit time in the sun, especially from 10 a.m. – 2 p.m.
• wear long-sleeve shirts, pants, hats, and sunglasses
• children under 6 months: Ask a docto

Other Information

■ Do not store this product in an inappropriate place such as high or low temperatures or under direct sun light

Questions

www.byselected.co.kr
byselected@naver.com
+82-70-8883-2525